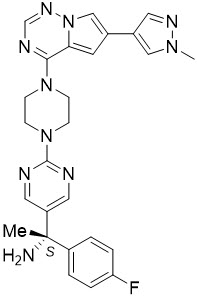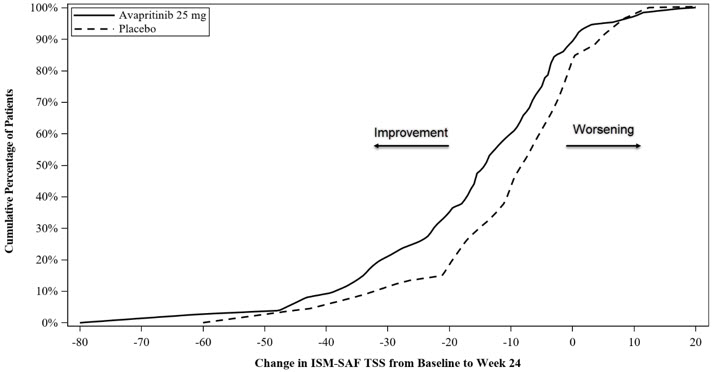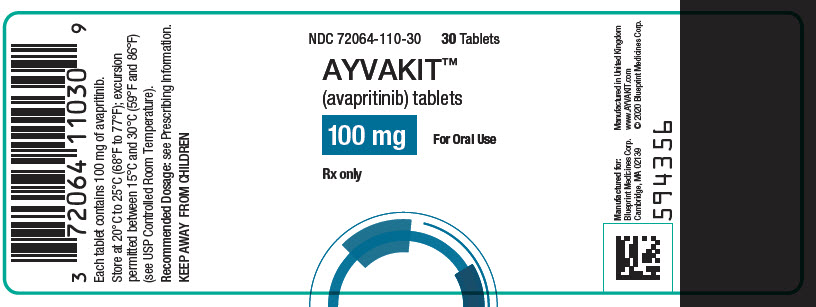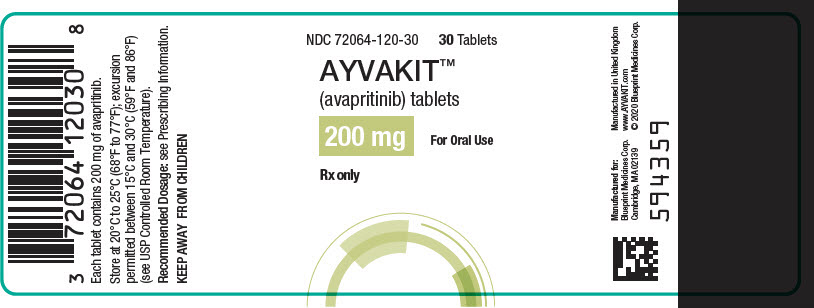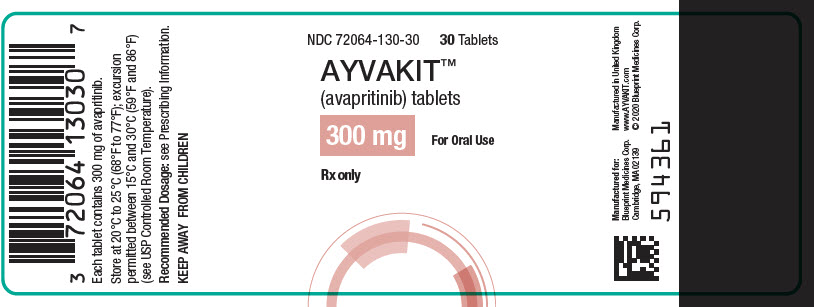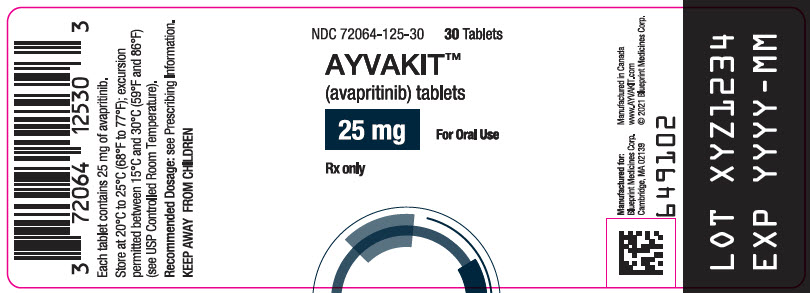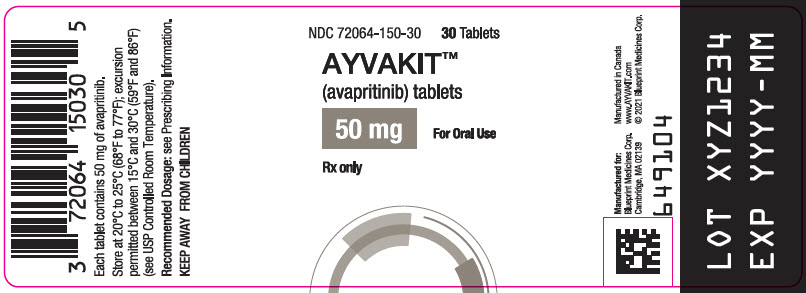 DRUG LABEL: Ayvakit
NDC: 72064-110 | Form: TABLET, FILM COATED
Manufacturer: Blueprint Medicines Corporation
Category: prescription | Type: HUMAN PRESCRIPTION DRUG LABEL
Date: 20250711

ACTIVE INGREDIENTS: avapritinib 100 mg/1 1
INACTIVE INGREDIENTS: Microcrystalline cellulose 101; Microcrystalline cellulose; Copovidone K25-31; Croscarmellose Sodium; Magnesium Stearate; Talc; Polyethylene Glycol 4000; Polyvinyl Alcohol (130000 MW); Titanium Dioxide; Shellac; Butyl Alcohol; FD&C Blue No. 1; Isopropyl Alcohol; Ferrosoferric Oxide; Propylene Glycol; Ammonia

HIGHLIGHTS OF PRESCRIBING INFORMATION

These highlights do not include all the information needed to use AYVAKIT safely and effectively. See full prescribing information for AYVAKIT.
AYVAKIT® (avapritinib) tablets, for oral use
Initial U.S. Approval: 2020

1 INDICATIONS AND USAGE

AYVAKIT is a kinase inhibitor indicated for:

Gastrointestinal Stromal Tumor (GIST)

- the treatment of adults with unresectable or metastatic GIST harboring a platelet-derived growth factor receptor alpha (PDGFRA) exon 18 mutation, including PDGFRA D842V mutations. (1.1, 2.2)

Advanced Systemic Mastocytosis (AdvSM)

- the treatment of adult patients with AdvSM. AdvSM includes patients with aggressive systemic mastocytosis (ASM), systemic mastocytosis with an associated hematological neoplasm (SM-AHN), and mast cell leukemia (MCL). (1.2)
- Limitations of Use: AYVAKIT is not recommended for the treatment of patients with AdvSM with platelet counts of less than 50 × 10^9/L (1.2)

Indolent Systemic Mastocytosis (ISM)

- the treatment of adult patients with ISM. (1.3)
- Limitations of Use: AYVAKIT is not recommended for the treatment of patients with ISM with platelet counts of less than 50 × 10^9/L (1.2)

2 DOSAGE AND ADMINISTRATION

- GIST: Select patients for treatment with AYVAKIT based on the presence of a PDGFRA exon 18 mutation. (2.2)
- GIST: The recommended dosage is 300 mg orally once daily. (2.2)
- AdvSM: The recommended dosage is 200 mg orally once daily. (2.3)
- ISM: The recommended dosage is 25 mg orally once daily. (2.4)
- Patients with severe hepatic impairment (Child-Pugh Class C): reduce dose of AYVAKIT. (2.7)

3 DOSAGE FORMS AND STRENGTHS

Tablets: 25 mg, 50 mg, 100 mg, 200 mg and 300 mg. (3)

4 CONTRAINDICATIONS

None. (4)

5 WARNINGS AND PRECAUTIONS

- Intracranial Hemorrhage: Permanently discontinue for any occurrence of any grade. (2.5, 5.1)
- Cognitive Effects: A broad spectrum of cognitive adverse reactions can occur in patients receiving AYVAKIT. In patients with GIST, AdvSM, or ISM depending on the severity, continue AYVAKIT at same dose, withhold and then resume at same or reduced dose upon improvement, or permanently discontinue. (2.5, 5.2)
- Photosensitivity: May cause photosensitivity reactions. Advise patients to limit direct ultraviolet exposure. (5.3)
- Embryo-Fetal Toxicity: Can cause fetal harm. Advise females and males of reproductive potential of the potential risk to a fetus and to use effective contraception. (5.4, 8.1, 8.3)

6 ADVERSE REACTIONS

The most common adverse reactions are:

- GIST (≥20% incidence): edema, nausea, fatigue/asthenia, cognitive impairment, vomiting, decreased appetite, diarrhea, increased lacrimation, abdominal pain, constipation, rash, dizziness, and hair color changes. (6.1)
- AdvSM (≥20% incidence): edema, diarrhea, nausea, and fatigue/asthenia. (6.1)
- ISM (≥10% incidence): eye edema, dizziness, peripheral edema and flushing. (6.1)

To report SUSPECTED ADVERSE REACTIONS, contact Blueprint Medicines Corporation at 1-888-258-7768 or FDA at 1-800-FDA-1088 or www.fda.gov/medwatch.

7 DRUG INTERACTIONS

- Strong and Moderate CYP3A Inhibitors: Avoid coadministration of AYVAKIT with strong and moderate CYP3A inhibitors. If coadministration of AYVAKIT with a moderate inhibitor cannot be avoided, reduce dose of AYVAKIT in patients with GIST or AdvSM. (2.6, 7.1)
- Strong and Moderate CYP3A Inducers: Avoid coadministration of AYVAKIT with strong and moderate CYP3A inducers. (7.1)
- Hormonal contraceptives containing ethinyl estradiol: See full prescribing information for dose-specific recommendations for concomitant use (7.2)

8 USE IN SPECIFIC POPULATIONS

Lactation: Advise not to breastfeed. (8.2)

FULL PRESCRIBING INFORMATION

1 INDICATIONS AND USAGE

1.1 PDGFRA Exon 18 Mutation-Positive Unresectable or Metastatic Gastrointestinal Stromal Tumor (GIST)

AYVAKIT® is indicated for the treatment of adults with unresectable or metastatic GIST harboring a platelet-derived growth factor receptor alpha (PDGFRA) exon 18 mutation, including PDGFRA D842V mutations [see Dosage and Administration (2.2)].

1.2 Advanced Systemic Mastocytosis (AdvSM)

AYVAKIT is indicated for the treatment of adult patients with advanced systemic mastocytosis (AdvSM). AdvSM includes patients with aggressive systemic mastocytosis (ASM), systemic mastocytosis with an associated hematological neoplasm (SM-AHN), and mast cell leukemia (MCL).

Limitations of Use:

AYVAKIT is not recommended for the treatment of patients with AdvSM with platelet counts of less than 50 × 10^9/L [see Warnings and Precautions (5.1)].

1.3 Indolent Systemic Mastocytosis (ISM)

AYVAKIT is indicated for the treatment of adult patients with indolent systemic mastocytosis (ISM).

Limitations of Use:

AYVAKIT is not recommended for the treatment of patients with ISM with platelet counts of less than 50 × 10^9/L [see Warnings and Precautions (5.1)].

2 DOSAGE AND ADMINISTRATION

2.1 Recommended Administration

Administer AYVAKIT orally on an empty stomach, at least 1 hour before or 2 hours after a meal [see Clinical Pharmacology (12.3)].

Do not make up for a missed dose within 8 hours of the next scheduled dose.

Do not repeat dose if vomiting occurs after AYVAKIT but continue with the next scheduled dose.

2.2 GIST Harboring PDGFRA Exon 18 Mutations

Select patients for treatment with AYVAKIT based on the presence of a PDGFRA exon 18 mutation [see Clinical Studies (14.1)]. An FDA-approved test for the detection of exon 18 mutations is not currently available.

The recommended dosage of AYVAKIT is 300 mg orally once daily in patients with GIST. Continue treatment until disease progression or unacceptable toxicity.

2.3 Advanced Systemic Mastocytosis

The recommended dosage of AYVAKIT is 200 mg orally once daily in patients with AdvSM. Continue treatment until disease progression or unacceptable toxicity.

2.4 Indolent Systemic Mastocytosis

The recommended dosage of AYVAKIT is 25 mg orally once daily in patients with ISM.

2.5 Dosage Modifications for Adverse Reactions

The recommended dosage reductions and modifications for adverse reactions are provided in Tables 1 and 2.

Table 1: Recommended Dosage Reductions for AYVAKIT for Adverse Reactions
Dose Reduction Level | Dosage in patients with GIST [Permanently discontinue AYVAKIT in patients with GIST who are unable to tolerate a dose of 100 mg once daily.] | Dosage in patients with AdvSM [Permanently discontinue AYVAKIT in patients with AdvSM who are unable to tolerate a dose of 25 mg once daily.]
First dose reduction | 200 mg once daily | 100 mg once daily
Second dose reduction | 100 mg once daily | 50 mg once daily
Third dose reduction | - | 25 mg once daily

Table 2: Recommended Dosage Modifications for AYVAKIT for Adverse Reactions
Adverse Reaction | Severity [Severity as defined by the National Cancer Institute Common Terminology Criteria for Adverse Events version 5.0] | Dosage Modification
Patients with GIST or AdvSM
Intracranial Hemorrhage [see Warnings and Precautions (5.1)] | Any grade | Permanently discontinue AYVAKIT.
Cognitive Effects [see Warnings and Precautions (5.2)] | Grade 1 | Continue AYVAKIT at same dose or reduced dose or withhold until improvement to baseline or resolution. Resume at same dose or reduced dose.
 | Grade 2 or Grade 3 | Withhold AYVAKIT until improvement to baseline, Grade 1, or resolution. Resume at same dose or reduced dose.
 | Grade 4 | Permanently discontinue AYVAKIT.
Other [see Adverse Reactions (6.1)] | Grade 3 or Grade 4 | Withhold AYVAKIT until improvement to less than or equal to Grade 2. Resume at same dose or reduced dose, as clinically appropriate.
Patients with AdvSM
Thrombocytopenia [see Warnings and Precautions (5.1)] | <50 × 10^9/L | Interrupt AYVAKIT until platelet count is ≥ 50 × 10^9/L, then resume at reduced dose (per Table 1). If platelet counts do not recover above 50 × 10^9/L, consider platelet support.

2.6 Concomitant Use of Strong and Moderate CYP3A Inhibitors

Avoid concomitant use of AYVAKIT with strong or moderate CYP3A inhibitors. If concomitant use with a moderate CYP3A inhibitor cannot be avoided, the starting dosage of AYVAKIT is as follows [see Drug Interactions (7.1)]:

- GIST: 100 mg orally once daily
- AdvSM: 50 mg orally once daily

For ISM, avoid concomitant use of AYVAKIT with strong or moderate CYP3A inhibitors.

2.7 Dosage Modifications for Severe Hepatic Impairment

A modified starting dosage of AYVAKIT is recommended for patients with severe hepatic impairment (Child-Pugh Class C) [see Use in Specific Populations (8.7)]:

- GIST: 200 mg orally once daily
- AdvSM: 100 mg orally once daily
- ISM: 25 mg orally every other day

3 DOSAGE FORMS AND STRENGTHS

Tablets:

- 25 mg, round, white film-coated tablet with debossed text. One side reads "BLU" and the other side reads "25".
- 50 mg, round, white film-coated tablet with debossed text. One side reads "BLU" and the other side reads "50".
- 100 mg, round, white film-coated, printed with blue ink "BLU" on one side and "100" on the other side.
- 200 mg, capsule shaped, white film-coated, printed with blue ink "BLU" on one side and "200" on the other side.
- 300 mg, capsule shaped, white film-coated, printed with blue ink "BLU" on one side and "300" on the other side.

4 CONTRAINDICATIONS

None.

5 WARNINGS AND PRECAUTIONS

5.1 Intracranial Hemorrhage

Serious intracranial hemorrhage may occur with AYVAKIT treatment; fatal events occurred in less than 1% of patients. Overall, intracranial hemorrhage (e.g., subdural hematoma, intracranial hemorrhage, and cerebral hemorrhage) occurred in 2.9% of the 749 patients with GIST or AdvSM who received AYVAKIT in clinical trials. No events of intracranial hemorrhage occurred in the 246 patients with ISM who received any dose of AYVAKIT in the PIONEER study.

Monitor patients closely for risk factors of intracranial hemorrhage which may include history of vascular aneurysm, intracranial hemorrhage or cerebrovascular accident within the prior year, concomitant use of anticoagulant drugs, or thrombocytopenia.

Symptoms of intracranial hemorrhage may include headache, nausea, vomiting, vision changes, or altered mental status. Advise patients to seek immediate medical attention for signs or symptoms of intracranial hemorrhage.

Permanently discontinue AYVAKIT if intracranial hemorrhage of any grade occurs [see Dosage and Administration (2.5)].

Gastrointestinal Stromal Tumors

Intracranial hemorrhage occurred in 3 of 267 patients (1.1%). Two (0.7%) of the events were Grade ≥ 3 and resulted in discontinuation of study drug. Events of intracranial hemorrhage occurred in a range from 1.7 months to 19.3 months after initiating AYVAKIT.

Advanced Systemic Mastocytosis

In patients with AdvSM who received AYVAKIT at 200 mg daily, intracranial hemorrhage occurred in 2 of 75 patients (2.7%) who had platelet counts ≥ 50 × 10^9/L prior to initiation of therapy and in 3 of 80 patients (3.8%) regardless of platelet counts.

In patients with AdvSM, a platelet count must be performed prior to initiating therapy; AYVAKIT is not recommended in patients with AdvSM with platelet counts < 50 × 10^9/L. Following treatment initiation, platelet counts must be performed every 2 weeks for the first 8 weeks regardless of baseline platelet count. After 8 weeks of treatment, monitor platelet counts every 2 weeks (or more frequently as clinically indicated) if values are less than 75 × 10^9/L, every 4 weeks if values are between 75 and 100 × 10^9/L, and as clinically indicated if values are greater than 100 × 10^9/L.

Manage platelet counts of < 50 × 10^9/L by treatment interruption or dose-reduction of AYVAKIT. Platelet support may be necessary [see Dosage and Administration (2.5)]. Dose-interruptions and dose-reductions for thrombocytopenia occurred in 20% and 22% of AYVAKIT-treated patients, respectively. Thrombocytopenia was generally reversible by reducing or interrupting AYVAKIT.

5.2 Cognitive Effects

Cognitive adverse reactions can occur in patients receiving AYVAKIT. These cognitive adverse reactions occurred in 33% of the 995 patients with GIST, AdvSM or ISM who received AYVAKIT in clinical trials. These adverse reactions were managed with dose interruption and/or reduction when needed.

Overall, 10% led to dose interruptions, 7% led to dose reductions and 2.2% led to permanent discontinuation of AYVAKIT treatment in patients with GIST, AdvSM or ISM.

Depending on the severity and indication, withhold AYVAKIT and then resume at the same dose or at a reduced dose upon improvement, or permanently discontinue AYVAKIT [see Dosage and Administration (2.5)].

Indolent Systemic Mastocytosis

Cognitive adverse reactions occurred in 7.8% of patients with ISM who received AYVAKIT + best supportive care versus 7% of patients who received placebo + best supportive care in the PIONEER study; <1% were Grade 3. The median time to onset of the first cognitive adverse reaction was 2.3 months (range: 0 to 5.4 months). Median time to improvement to Grade 1 or complete resolution was 2.1 months (range: 0.4 to 2.1 months).

Gastrointestinal Stromal Tumors

Cognitive adverse reactions occurred in 41% of 601 patients with GIST who received AYVAKIT; 5% were Grade ≥ 3. Memory impairment occurred in 21% of patients; <1% of these events were Grade 3. Cognitive disorder occurred in 12% of patients; 1.2% of these events were Grade 3. Confusional state occurred in 6% of patients; <1% of these events were Grade 3. Amnesia occurred in 3% of patients; <1% of these events were Grade 3. Somnolence and speech disorder occurred in 2% of patients; none of these events were Grade 3. Other events occurred in less than 2% of patients.

The median time to onset of the first cognitive adverse reaction was 8.4 weeks (range: 1 day to 4 years). Among patients who experienced a cognitive effect of Grade 2 or worse (impacting activities of daily living), the median time to improvement to Grade 1 or complete resolution was 7.9 weeks. Overall, 2.7% of all patients who received AYVAKIT required permanent discontinuation for a cognitive adverse reaction, 13.5% required a dosage interruption, and 8.5% required dose reduction.

Advanced Systemic Mastocytosis

Cognitive adverse reactions occurred in 28% of 148 patients with AdvSM who received AYVAKIT; 3% were Grade ≥ 3. Memory impairment occurred in 16% of patients; all events were Grade 1 or 2. Cognitive disorder occurred in 10% of patients; <1% of these events were Grade 3. Confusional state occurred in 6% of patients; <1% of these events were Grade 3. Other events occurred in less than 2% of patients.

The median time to onset of the first cognitive adverse reaction was 13.3 weeks (range: 1 day to 1.8 years). Among patients who experienced a cognitive effect of Grade 2 or worse (impacting activities of daily living), the median time to improvement to Grade 1 or complete resolution was 8.1 weeks. Overall, 2% of all patients who received AYVAKIT required permanent discontinuation for a cognitive adverse reaction, 8.1% required a dosage interruption, and 8.8% required dose reduction.

5. 3 Photosensitivity

AYVAKIT may cause photosensitivity reactions. In all patients treated with AYVAKIT in clinical trials (n=1049), photosensitivity reactions occurred in 2.5% of patients. Advise patients to limit direct ultraviolet exposure during treatment with AYVAKIT and for one week after discontinuation of treatment.

5.4 Embryo-Fetal Toxicity

Based on findings from animal studies and its mechanism of action, AYVAKIT can cause fetal harm when administered to pregnant women. Oral administration of avapritinib during the period of organogenesis was teratogenic and embryotoxic in rats at exposures approximately 31.4, 6.3 and 2.7 times the human exposure based on area under the curve (AUC) at the 25 mg, 200 mg, and 300 mg dose, respectively.

Advise pregnant women of the potential risk to a fetus. Advise females and males of reproductive potential to use effective contraception during treatment with AYVAKIT and for 6 weeks after the final dose [see Use in Specific Populations (8.1, 8.3)].

6 ADVERSE REACTIONS

The following clinically significant adverse reactions are described elsewhere in the labeling:

- Intracranial hemorrhage [see Warnings and Precautions (5.1)]
- Cognitive effects [see Warnings and Precautions (5.2)]
- Photosensitivity [see Warnings and Precautions (5.3)]

6.1 Clinical Trials Experience

Because clinical trials are conducted under widely varying conditions, adverse reaction rates observed in the clinical trials of a drug cannot be directly compared to rates in the clinical trials of another drug and may not reflect the rates observed in practice.

The data in the WARNINGS AND PRECAUTIONS reflect exposure to AYVAKIT at 25 mg to 600 mg orally once daily in 995 patients enrolled in one of five clinicals trials conducted in patients with advanced malignancies and systemic mastocytosis, including NAVIGATOR, EXPLORER, PATHFINDER and PIONEER [see Clinical Studies (14.1, 14.2, 14.3)]. These patients included 601 patients with GIST, 148 patients with AdvSM and 246 patients with ISM. Among the 995 patients receiving AYVAKIT, 54% were exposed for 6 months or longer and 26% were exposed for greater than 1 year.

Gastrointestinal Stromal Tumors

Unresectable or Metastatic GIST

The safety of AYVAKIT in patients with unresectable or metastatic GIST was evaluated in NAVIGATOR [see Clinical Studies (14.1)]. The trial excluded patients with history of cerebrovascular accident or transient ischemic attacks, known risk of intracranial bleeding, and metastases to the brain. Patients received AYVAKIT 300 mg or 400 mg orally once daily (n = 204). Among patients receiving AYVAKIT, 56% were exposed for 6 months or longer and 44% were exposed for greater than one year.

The median age of patients who received AYVAKIT was 62 years (range: 29 to 90 years), 60% were <65 years, 62% were male, and 69% were White. Patients had received a median of 3 prior kinase inhibitors (range: 0 to 7).

Serious adverse reactions occurred in 52% of patients receiving AYVAKIT. Serious adverse reactions occurring in ≥1% of patients who received AYVAKIT were anemia (9%), abdominal pain (3%), pleural effusion (3%), sepsis (3%), gastrointestinal hemorrhage (2%), vomiting (2%), acute kidney injury (2%), pneumonia (1%), and tumor hemorrhage (1%). Fatal adverse reactions occurred in 3.4% of patients. Fatal adverse reactions that occurred in more than one patient were sepsis and tumor hemorrhage (1% each).

Permanent discontinuation due to adverse reactions occurred in 16% of patients who received AYVAKIT. Adverse reactions requiring permanent discontinuation in more than one patient were fatigue, abdominal pain, vomiting, sepsis, anemia, acute kidney injury, and encephalopathy.

Dosage interruptions due to an adverse reaction occurred in 57% of patients who received AYVAKIT. Adverse reactions requiring dosage interruption in >2% of patients who received AYVAKIT were anemia, fatigue, nausea, vomiting, hyperbilirubinemia, memory impairment, diarrhea, cognitive disorder, and abdominal pain.

Dose reduction due to an adverse reaction occurred in 49% of patients who received AYVAKIT. Median time to dose reduction was 9 weeks. Adverse reactions requiring dosage reduction in more than 2% of patients who received AYVAKIT were fatigue, anemia, hyperbilirubinemia, memory impairment, nausea, and periorbital edema.

The most common adverse reactions (≥ 20%) were edema, nausea, fatigue/asthenia, cognitive impairment, vomiting, decreased appetite, diarrhea, increased lacrimation, abdominal pain, constipation, rash, dizziness, and hair color changes. Table 5 summarizes the adverse reactions observed in NAVIGATOR.

Table 5. Adverse Reactions (≥ 10%) in Patients with GIST Receiving AYVAKIT in NAVIGATOR
Adverse Reactions [Per National Cancer Institute Common Terminology Criteria for Adverse Events (CTCAE) version 4.03 and 5.0] | AYVAKIT N=204
Adverse Reactions [Per National Cancer Institute Common Terminology Criteria for Adverse Events (CTCAE) version 4.03 and 5.0] | All Grades % | Grade ≥ 3 %
General
Edema [Edema includes face swelling, conjunctival edema, eye edema, eyelid edema, orbital edema, periorbital edema, face edema, mouth edema, pharyngeal edema, peripheral edema, edema, generalized edema, localized edema, peripheral swelling, testicular edema.] | 72 | 2
Fatigue/asthenia | 61 | 9
Pyrexia | 14 | 0.5
Gastrointestinal
Nausea | 64 | 2.5
Vomiting | 38 | 2
Diarrhea | 37 | 4.9
Abdominal pain [Abdominal pain includes abdominal pain, upper abdominal pain, abdominal discomfort, lower abdominal pain, abdominal tenderness, and epigastric discomfort.] | 31 | 6
Constipation | 23 | 1.5
Dyspepsia | 16 | 0
Nervous System
Cognitive impairment [Cognitive impairment includes memory impairment, cognitive disorder, confusional state, disturbance in attention, amnesia, mental impairment, mental status changes, encephalopathy, dementia, abnormal thinking, mental disorder, and retrograde amnesia.] | 48 | 4.9
Dizziness | 22 | 0.5
Headache | 17 | 0.5
Sleep disorders [Sleep disorders includes insomnia, somnolence, and sleep disorder.] | 16 | 0
Taste effects [Taste effects include dysgeusia and ageusia.] | 15 | 0
Mood disorders [Mood disorders includes agitation, anxiety, depression, depressed mood, dysphoria, irritability, mood altered, nervousness, personality change, and suicidal ideation.] | 13 | 1
Metabolism and nutrition
Decreased appetite | 38 | 2.9
Eye
Increased lacrimation | 33 | 0
Skin and subcutaneous tissue
Rash [Rash includes rash, rash maculo-papular, rash erythematous, rash macular, rash generalized, and rash papular.] | 23 | 2.1
Hair color changes | 21 | 0.5
Alopecia | 13 | 0
Respiratory, thoracic and mediastinal
Dyspnea | 17 | 2.5
Pleural effusion | 12 | 2
Investigations
Weight decreased | 13 | 1

Clinically relevant adverse reactions occurring in <10% of patients were:

Vascular: hypertension (8%)

Endocrine: thyroid disorders (hyperthyroid, hypothyroid) (3%)

Skin and subcutaneous: palmar-plantar erythrodysesthesia (1%)

Table 6 summarizes the laboratory abnormalities observed in NAVIGATOR.

Table 6. Select Laboratory Abnormalities (≥ 10%) Worsening from Baseline in Patients with GIST Receiving AYVAKIT in NAVIGATOR
Laboratory Abnormality | AYVAKIT [The denominator used to calculate the rate varied from 154 to 201 based on the number of patients with a baseline value and at least one post-treatment value.] N=204
Laboratory Abnormality | All Grades (%) | Grade ≥ 3 (%)
Hematology
Decreased hemoglobin | 81 | 28
Decreased leukocytes | 62 | 5
Decreased neutrophils | 43 | 6
Decreased platelets | 27 | 0.5
Increased INR | 24 | 0.6
Increased activated partial thromboplastin time | 13 | 0
Chemistry
Increased bilirubin | 69 | 9
Increased aspartate aminotransferase | 51 | 1.5
Decreased phosphate | 49 | 13
Decreases potassium | 34 | 6
Decreased albumin | 31 | 2
Decreased magnesium | 29 | 1
Increased creatinine | 29 | 0
Decreased sodium | 28 | 7
Increased alanine aminotransferase | 19 | 0.5
Increased alkaline phosphatase | 14 | 1

Advanced Systemic Mastocytosis

The safety of AYVAKIT in patients with AdvSM was evaluated in EXPLORER and PATHFINDER [see Clinical Studies (14.2)]. Patients received a starting dose of AYVAKIT ranging from 30 mg to 400 mg orally once daily (n = 131), including 80 patients who received the recommended starting dose of 200 mg once daily. Among patients receiving AYVAKIT, 70% were treated for 6 months or longer and 37% were exposed for greater than one year.

The median age of patients who received AYVAKIT was 68 years (range: 31 to 88 years), 38% were <65 years, 57% were male, and 88% were White.

Serious adverse reactions occurred in 34% of patients receiving the recommended starting dose of 200 mg once daily and in 50% of patients receiving AYVAKIT at all doses. Serious adverse reactions occurring in ≥1% of patients who received AYVAKIT were anemia (5%), subdural hematoma (4%), pleural effusion, ascites and pneumonia (3% each), acute kidney injury, gastrointestinal hemorrhage, intracranial hemorrhage, encephalopathy, gastric hemorrhage, large intestine perforation, pyrexia, and vomiting (2% each). Fatal adverse reactions occurred in 2.5% of patients receiving the recommended starting dose of 200 mg once daily and in 5.3% of patients receiving AYVAKIT at all doses. No specific adverse reaction leading to death was reported in more than one patient.

Permanent discontinuation due to adverse reactions occurred in 10% of patients receiving the recommended starting dose of 200 mg once daily and in 15% of patients who received AYVAKIT at all doses. Of patients receiving 200 mg once daily, subdural hematoma was the only adverse reaction requiring permanent discontinuation in more than one patient.

Dosage interruptions due to an adverse reaction occurred in 60% of patients receiving the recommended starting dose of 200 mg once daily and in 67% of patients who received AYVAKIT at all doses. Adverse reactions requiring dosage interruption in >2% of patients who received AYVAKIT at 200 mg once daily were thrombocytopenia, neutropenia, neutrophil count decreased, platelet count decreased, anemia, white blood cell decreased, cognitive disorder, blood alkaline phosphatase increased, and edema peripheral.

Dose reduction due to an adverse reaction occurred in 68% of patients receiving the recommended starting dose of 200 mg once daily and 70% of patients who received AYVAKIT at all doses. Median time to dose reduction was 1.7 months. Adverse reactions requiring dosage reduction in more than 2% of patients who received AYVAKIT at 200 mg once daily were thrombocytopenia, neutropenia, edema peripheral, neutrophil count decreased, platelet count decreased, periorbital edema, cognitive disorder, anemia, fatigue, arthralgia, blood alkaline phosphatase increased, and white blood cell count decreased.

The most common adverse reactions (≥ 20%) at all doses were edema, diarrhea, nausea, and fatigue/asthenia. Table 7 summarizes the adverse reactions observed in EXPLORER and PATHFINDER.

Table 7. Adverse Reactions (≥ 10%) in Patients with AdvSM Receiving AYVAKIT in EXPLORER and PATHFINDER
Adverse Reactions [Per National Cancer Institute Common Terminology Criteria for Adverse Events (CTCAE) version 4.03 and 5.0] | AYVAKIT (200 mg once daily) N=80
Adverse Reactions [Per National Cancer Institute Common Terminology Criteria for Adverse Events (CTCAE) version 4.03 and 5.0] | All Grades % | Grade ≥ 3 %
General
Edema [Edema includes face swelling, eyelid edema, orbital edema, periorbital edema, face edema, peripheral edema, edema, generalized edema, and peripheral swelling.] | 79 | 5
Fatigue/asthenia | 23 | 4
Gastrointestinal
Diarrhea | 28 | 1
Nausea | 24 | 1
Vomiting | 18 | 3
Abdominal pain [Abdominal pain includes abdominal pain, upper abdominal pain, and abdominal discomfort.] | 14 | 1
Constipation | 11 | 0
Nervous system
Headache | 15 | 0
Cognitive effects [Cognitive effects include memory impairment, cognitive disorder, confusional state, delirium, and disorientation.] | 14 | 1
Taste effects [Taste effects include dysgeusia.] | 13 | 0
Dizziness | 13 | 0
Musculoskeletal and connective tissue
Arthralgia | 10 | 1
Respiratory, thoracic and mediastinal
Epistaxis | 11 | 0

Clinically relevant adverse reactions occurring in <10% of patients were:

Cardiac: cardiac failure (2.5%), and cardiac failure congestive (1.3%)

Gastrointestinal: ascites (5%), gastrointestinal hemorrhage (1.3%), and large intestine perforation (1.3%)

Hepatobiliary: cholelithiasis (1.3%)

Infections and infestations: upper respiratory tract infection (6%), urinary tract infection (6%), and herpes zoster (2.5%)

Vascular: flushing (3.8%), hypertension (3.8%), hypotension (3.8%), and hot flush (2.5%)

Nervous: insomnia (6%)

Musculoskeletal and connective tissue: pain in extremity (6%)

Respiratory, thoracic and mediastinal: dyspnea (9%), and cough (2.5%)

Skin and subcutaneous tissue: rash [Grouped terms] (8%), alopecia (9%), pruritus (8%), and hair color changes (6%)

Metabolism and nutrition: decreased appetite (8%)

Eye: lacrimation increased (9%)

Laboratory abnormality: decreased phosphate (9%)

Rash includes rash and rash maculo-papular

Table 8 summarizes the laboratory abnormalities observed in EXPLORER and PATHFINDER.

Table 8. Select Laboratory Abnormalities (≥ 10%) Worsening from Baseline in Patients with AdvSM Receiving AYVAKIT in EXPLORER and PATHFINDER
Laboratory Abnormality | AYVAKIT (200 mg once daily) N=80
Laboratory Abnormality | All Grades (%) | Grade ≥ 3 (%)
Hematology
Decreased platelets | 64 | 21
Decreased hemoglobin | 55 | 23
Decreased neutrophils | 54 | 25
Decreased lymphocytes | 34 | 11
Increased activated partial thromboplastin time | 14 | 1
Increased lymphocytes | 10 | 0
Chemistry
Decreased calcium | 50 | 3
Increased bilirubin | 41 | 3
Increased aspartate aminotransferase | 38 | 1
Decreased potassium | 26 | 4
Increased alkaline phosphatase | 24 | 5
Increased creatinine | 20 | 0
Increased alanine aminotransferase | 18 | 1
Decreased sodium | 18 | 1
Decreased albumin | 15 | 1
Decreased magnesium | 14 | 1
Increased potassium | 11 | 0

Other Clinically Relevant Adverse Reactions in <10% of patients

In the pooled GIST and AdvSM safety populations, photosensitivity occurred in 2.5% of patients [see Warnings and Precautions (5.3)].

Indolent Systemic Mastocytosis

The safety of AYVAKIT in patients with ISM was evaluated in PIONEER [see Clinical Studies (14.3)]. Patients received AYVAKIT 25 mg orally once daily with best supportive care (n = 141) or placebo once daily with best supportive care (n = 71).

Serious adverse reactions occurred in 1 patient (0.7%) who received AYVAKIT due to pelvic hematoma.

Permanent discontinuation of AYVAKIT due to an adverse reaction occurred in 1 patient (0.7%) due to dyspnea and dizziness.

Dosage interruptions of AYVAKIT due to an adverse reaction occurred in 5% of patients. Adverse reactions which required dosage interruption included dizziness, blood alkaline phosphatase increased, dyspnea, face edema, pelvic hematoma, liver transaminase increased and respiratory tract infection (1 patient each).

Table 9 summarizes the frequency of adverse reactions in the PIONEER study. The most common adverse reactions (≥ 10%) in the AYVAKIT group were eye edema, dizziness, peripheral edema and flushing. Of all adverse reactions, 55% were Grade 1, 38% were Grade 2 and 7% were Grade 3. Among patients with edema adverse reactions, 95% were Grade 1 and 5% were Grade 2. Among patients with hemorrhage adverse reactions, 86% were Grade 1 and 14% were Grade 2.

Table 9. Adverse Reactions Occurring in AYVAKIT-Treated Patients with Indolent Systemic Mastocytosis During PIONEER Trial
Adverse Reactions [Adverse reactions that occurred in ≥5% of AYVAKIT-treated patients and ≥2% more than placebo-treated patients.] , [Per National Cancer Institute Common Terminology Criteria for Adverse Events (CTCAE) version 5.0] | AYVAKIT (25 mg once daily) + BSC N=141 % | Placebo + BSC N=71 %
Eye edema [Eye edema includes periorbital edema, eye edema, swelling of eyelid, orbital edema, eye swelling, eyelid edema and eyelid ptosis.] | 13 | 7
Dizziness [Term includes several similar terms.] | 13 | 10
Peripheral edema | 12 | 6
Flushing | 11 | 4
Respiratory tract infection [Respiratory tract infection includes pneumonia, upper respiratory tract infection, bronchitis and respiratory tract infection.] | 8 | 1
Face edema | 7 | 1
Rash | 6 | 4
Liver transaminase increased | 6 | 3
Insomnia | 6 | 3
Hematoma [Hematoma includes contusion, hematoma and pelvic hematoma.] | 6 | 1
Blood alkaline phosphatase increased | 6 | 1
Hemorrhage [Hemorrhage includes epistaxis, gingival bleeding, hematochezia, rectal hemorrhage, retinal hemorrhage.] | 5 | 3
Abbreviations: BSC=best supportive care

Clinically relevant adverse reactions occurring in <5% of patients were:

Skin and subcutaneous tissue: photosensitivity (2.8%)

7 DRUG INTERACTIONS

7.1 Effects of Other Drugs on AYVAKIT

Strong and Moderate CYP3A Inhibitors

Coadministration of AYVAKIT with a strong or moderate CYP3A inhibitor increases avapritinib plasma concentrations [see Clinical Pharmacology (12.3)], which may increase the incidence and severity of adverse reactions of AYVAKIT. Avoid coadministration of AYVAKIT with strong or moderate CYP3A inhibitors. If coadministration of AYVAKIT with a moderate CYP3A inhibitor cannot be avoided, reduce the dose of AYVAKIT [see Dosage and Administration (2.6)].

Strong and Moderate CYP3A Inducers

Coadministration of AYVAKIT with a strong or moderate CYP3A inducer decreases avapritinib plasma concentrations [see Clinical Pharmacology (12.3)], which may decrease efficacy of AYVAKIT. Avoid coadministration of AYVAKIT with strong or moderate CYP3A inducers.

7.2 Effects of AYVAKIT on Other Drugs

Coadministration of AYVAKIT with ethinyl estradiol-containing contraceptives may increase the exposure of ethinyl estradiol, which may lead to increased risk of ethinyl estradiol-associated adverse reactions [see Clinical Pharmacology (12.3)].

If the patient is unable to use or tolerate an effective nonhormonal contraceptive or an effective hormonal contraceptive without estrogen, use a formulation of ethinyl estradiol containing 20 mcg or less unless a higher dose is necessary.

8 USE IN SPECIFIC POPULATIONS

8.1 Pregnancy

Risk Summary

Based on findings from animal studies and its mechanism of action [see Clinical Pharmacology (12.1)], AYVAKIT can cause fetal harm when administered to a pregnant woman. There are no available data on AYVAKIT use in pregnant women. Oral administration of avapritinib to pregnant rats during the period of organogenesis was teratogenic and embryotoxic at exposure levels approximately 31.4, 6.3 and 2.7 times the human exposure based on AUC at the 25 mg, 200 mg and 300 mg dose, respectively (see Data). Advise pregnant women of the potential risk to a fetus.

In the U.S. general population, the estimated background risk of major birth defects and miscarriage in clinically recognized pregnancies is 2-4% and 15-20%, respectively.

Data

Animal Data

In a reproductive toxicity study, administration of avapritinib to rats during the period of organogenesis resulted in decreased fetal body weights, post-implantation loss, and increases in visceral (hydrocephaly, septal defect, and stenosis of the pulmonary trunk) and skeletal (sternum) malformations at doses greater than or equal to 10 mg/kg/day (approximately 31.4, 6.3 and 2.7 times the human exposure based on AUC at the 25 mg, 200 mg and 300 mg dose, respectively).

8.2 Lactation

Risk Summary

There are no data on the presence of avapritinib or its metabolites in human milk or the effects of avapritinib on the breastfed child or milk production. Because of the potential for serious adverse reactions in breastfed children, advise women not to breastfeed during treatment with AYVAKIT and for 2 weeks following the final dose.

8.3 Females and Males of Reproductive Potential

Pregnancy Testing

Verify the pregnancy status of females of reproductive potential prior to initiating AYVAKIT [see Use in Specific Populations (8.1)].

Contraception

AYVAKIT can cause fetal harm when administered to pregnant women [see Use in Specific Populations (8.1)].

Females

Advise females of reproductive potential to use effective contraception during treatment with AYVAKIT and for 6 weeks after the final dose [see Drug Interactions (7.2)].

Males

Advise males with female partners of reproductive potential to use effective contraception during treatment with AYVAKIT and for 6 weeks after the final dose.

Infertility

Females

Based on findings from animal studies, AYVAKIT may impair female fertility. These findings were not reversible within a two month recovery period [see Nonclinical Toxicology (13.1)].

Males

Based on findings from animal studies, AYVAKIT may impair male fertility. These findings were not reversible within a two month recovery period [see Nonclinical Toxicology (13.1)].

8.4 Pediatric Use

The safety and effectiveness of AYVAKIT in pediatric patients have not been established.

8.5 Geriatric Use

Of the 204 patients with unresectable or metastatic GIST who received AYVAKIT in NAVIGATOR, 40% were 65 years or older, while 6% were 75 years and older. Of the 131 patients with AdvSM who received AYVAKIT in EXPLORER and in PATHFINDER, 62% were 65 years or older, while 21% were 75 years and older. Of the 141 patients with ISM who received AYVAKIT in PIONEER, 6% were 65 years or older, while <1% were 75 years and older. No overall differences in safety or efficacy were observed between these patients and younger adult patients.

8.6 Renal Impairment

No dose adjustment is recommended for patients with mild or moderate renal impairment [creatinine clearance (CLcr) 30 to 89 mL/min estimated by Cockcroft-Gault]. The recommended dose of AYVAKIT has not been established for patients with severe renal impairment (CLcr 15 to 29 mL/min) or end-stage renal disease (CLcr <15 mL/min) [see Clinical Pharmacology (12.3)].

8.7 Hepatic Impairment

No dose adjustment is recommended for patients with mild [total bilirubin ≤ upper limit of normal (ULN) and aspartate aminotransferase (AST) > ULN or total bilirubin > 1 to 1.5 times ULN and any AST], or moderate [total bilirubin >1.5 to 3 times ULN and any AST] hepatic impairment. Unbound AUC0-INF was 61% higher in subjects with severe hepatic impairment (Child-Pugh Class C) as compared to matched healthy subjects with normal hepatic function. A lower starting dose is recommended in patients with severe hepatic impairment [see Dosage and Administration (2.7)].

11 DESCRIPTION

Avapritinib is a kinase inhibitor with the chemical name (S)-1-(4-fluorophenyl)-1-(2-(4-(6-(1-methyl-1H-pyrazol-4-yl)pyrrolo[2,1-f][1,2,4]triazin-4-yl)piperazin-yl)pyrimidin-5-yl)ethan-1-amine. The molecular formula is C26H27FN10, and the molecular weight is 498.57 g/mol. Avapritinib has the following chemical structure:

The solubility of avapritinib in 0.1N HCl (pH 1.0) and buffer solutions at pH 2.5, 4.0, and 7.0 (at 25°C) is 3.6 mg/mL, 0.14 mg/mL, 0.07 mg/mL and <0.001 mg/mL respectively, indicating a decrease in solubility with increasing pH.

AYVAKIT (avapritinib) film-coated tablets for oral use are supplied with five strengths that contain 25 mg, 50 mg, 100 mg, 200 mg or 300 mg of avapritinib. The tablets also contain inactive ingredients: copovidone, croscarmellose sodium, magnesium stearate, and microcrystalline cellulose. The tablet coating consists of polyethylene glycol, polyvinyl alcohol, talc, and titanium dioxide. The blue printing ink, used only for avapritinib 100 mg, 200 mg and 300 mg strength tablets, contains ammonium hydroxide, black iron oxide, esterified shellac, FD&C blue 1, isopropyl alcohol, n-butyl alcohol, propylene glycol, and titanium dioxide.

12 CLINICAL PHARMACOLOGY

12.1 Mechanism of Action

Avapritinib is a tyrosine kinase inhibitor that targets KIT D816V, PDGFRA and PDGFRA D842 mutants as well as multiple KIT exon 11, 11/17 and 17 mutants with half maximal inhibitory concentrations (IC50s) less than 25 nM in biochemical assays. Certain mutations in PDGFRA and KIT can result in the autophosphorylation and constitutive activation of these receptors which can contribute to tumor and mast cell proliferation. Other potential targets for avapritinib include wild type KIT, PDGFRB, and CSFR1.

In cellular assays, avapritinib inhibited the autophosphorylation of KIT D816V with an IC50 of 4 nM, approximately 48-fold lower concentration than wild-type KIT. In cellular assays, avapritinib inhibited the proliferation in KIT mutant cell lines, including a murine mastocytoma cell line and a human mast cell leukemia cell line. Avapritinib also showed growth inhibitory activity in a xenograft model of murine mastocytoma with KIT exon 17 mutation.

Avapritinib inhibited the autophosphorylation of PDGFRA D842V, a mutation associated with resistance to approved kinase inhibitors, with an IC50 of 30 nM. Avapritinib also had anti-tumor activity in mice implanted with an imatinib-resistant patient-derived xenograft model of human GIST with activating KIT exon 11/17 mutations.

12.2 Pharmacodynamics

Exposure-Response Relationships

Gastrointestinal Stromal Tumors or Advanced Systemic Mastocytosis

Based on the data from four clinicals trials conducted in patients with advanced malignancies and AdvSM, including NAVIGATOR, EXPLORER, and PATHFINDER, higher exposure was associated with increased risk of Grade ≥ 3 related adverse effects, any Grade pooled cognitive adverse effects, Grade ≥ 2 pooled cognitive adverse effects, and Grade ≥ 2 pooled edema adverse effects over the dose range of 30 mg to 400 mg (0.1 to 1.33 times the recommended dose for GIST and 0.15 to 2 times the recommended dose for AdvSM) once daily.

Based on exposure and efficacy data from EXPLORER and PATHFINDER (n=84), higher avapritinib exposure was associated with faster time to response over the dose range of 30 mg to 400 mg (0.15 to 2 times the recommended dose for AdvSM) once daily.

Cardiac Electrophysiology

The effect of AYVAKIT on the QTc interval was evaluated in an open-label, single-arm study in 27 patients administered doses of 300 mg or 400 mg (12 to 16 times the lowest recommended 25 mg dose, 1.33 times the highest recommended 300 mg dose) once daily. No large mean increase in QTc (i.e.> 20 ms) was detected at the mean steady state maximum concentration (Cmax) of 899 ng/mL.

12.3 Pharmacokinetics

Avapritinib Cmax and AUC increased approximately proportionally over the dose range of 25 mg to 400 mg once daily. Steady state concentrations of avapritinib were reached prior to day 15 following daily dosing. Steady state pharmacokinetic parameters per recommended dosing regimen are described in Table 10.

Table 10. Steady State Pharmacokinetic Parameters of AYVAKIT Following Different Dosing Regimen
Pharmacokinetic Parameters | 25 mg once daily (ISM) | 200 mg once daily (AdvSM) | 300 mg once daily (GIST)
Cmax (ng/mL) Geometric Mean (CV%) | 70.2 (47.8 %, n=9) | 377 (62%, n=18) | 813 (52%, n=110)
AUC0-24h (h∙ng/mL) Geometric Mean (CV%) | 1330 (49.5 %, n = 9) | 6600 (54%, n=16) | 15400 (48%, n=110)
Mean accumulation ratio of AUC 0-24h | 4.06 (n=9) | 6.41 (n=9) | 3.82 (n=34)
Abbreviations: CV%=coefficient of variation

Absorption

The median time to peak concentration (Tmax) ranged from 2 to 4 hours following single doses of avapritinib.

Effect of Food

The Cmax of avapritinib was increased by 59% and the AUC0-INF was increased by 29% when AYVAKIT was taken with a high-calorie, high-fat meal (approximately 909 calories, 58 grams carbohydrate, 56 grams fat and 43 grams protein) compared to those in the fasted state.

Distribution

The mean (CV %) apparent volume of distribution of avapritinib is 1310 L (51.5%) at 300 mg in patients with GIST, 1900 L (43.2%) at 200 mg in patients with AdvSM, and 1400 L (59.1%) at 25 mg in patients with ISM. In vitro protein binding of avapritinib is 98.8% and is independent of concentration. The blood-to-plasma ratio is 0.95.

Elimination

The mean plasma elimination half-life of avapritinib was 32 to 57 hours in patients with GIST, 20 to 39 hours in patients with AdvSM, and 38 to 45 hours in patients with ISM. The steady state mean (CV%) apparent oral clearance of avapritinib is 21.8 L/h (54.9%) at 300 mg in patients with GIST, 40.3 L/h (86.0%) at 200 mg in patients with AdvSM, and 21.6 L/h (58.1%) at 25 mg in patients with ISM.

Metabolism

Avapritinib is primarily metabolized by CYP3A4, CYP3A5 and to a lesser extent by CYP2C9 in vitro. Following a single oral dose of approximately 310 mg of radiolabeled avapritinib to healthy subjects, unchanged avapritinib (49%) and its metabolites M690 (hydroxy glucuronide; 35%) and M499 (oxidative deamination; 14%) were the major circulating compounds. The formation of the glucuronide M690 is catalyzed mainly by UGT1A3. Following oral administration of AYVAKIT 300 mg once daily in patients, the steady state AUC of M499 is approximately 80% of the AUC of avapritinib. M499 is not likely to contribute to efficacy at the recommended dose of avapritinib.

Excretion

Following a single oral dose of approximately 310 mg of radiolabeled avapritinib to healthy subjects, 70% of the radioactive dose was recovered in feces (11% unchanged) and 18% in urine (0.23% unchanged).

Specific Populations

No clinically significant differences in the pharmacokinetics of avapritinib were observed based on age (18 to 90 years), sex, race (White, Black, or Asian), body weight (39.5 to 156.3 kg), mild to moderate (CLcr 30 to 89 mL/min estimated by Cockcroft-Gault) renal impairment, or mild (total bilirubin ≤ ULN and AST > ULN or total bilirubin > 1 to 1.5 times ULN and any AST) to moderate (total bilirubin > 1.5 to 3 times ULN and any AST) hepatic impairment. In a dedicated hepatic impairment study following a single oral dose administration of 100 mg avapritinib, the mean unbound AUC was 61% higher in subjects with severe hepatic impairment (Child-Pugh Class C) as compared to matched healthy subjects with normal hepatic function. The effect of severe renal impairment (CLcr 15 to 29 mL/min) and end-stage renal disease (CLcr < 15 mL/min) on the pharmacokinetics of avapritinib is unknown.

Drug Interaction Studies

Clinical Studies and Model-Informed Approaches

Effect of Strong and Moderate CYP3A Inhibitors on Avapritinib: Coadministration of AYVAKIT 300 mg once daily with itraconazole 200 mg once daily (a strong CYP3A inhibitor) is predicted to increase avapritinib AUC by 600% at steady state.

Coadministration of AYVAKIT 300 mg once daily with fluconazole 200 mg once daily (a moderate CYP3A inhibitor) is predicted to increase avapritinib AUC by 210% at steady state [see Dosage and Administration (2.6), Drug Interactions (7.1)].

Effect of Strong and Moderate CYP3A Inducers on Avapritinib: Coadministration of AYVAKIT 400 mg as a single dose with rifampin 600 mg once daily (a strong CYP3A inducer) decreased avapritinib Cmax by 74% and AUC0-INF by 92%.

Coadministration of AYVAKIT 300 mg once daily with efavirenz 600 mg once daily (a moderate CYP3A inducer) is predicted to decrease avapritinib Cmax by 55% and AUC by 62% at steady state [see Drug Interactions (7.1)].

Effect of Acid-Reducing Agents on Avapritinib: No clinically significant differences in the pharmacokinetics of avapritinib were identified when coadministered with gastric acid reducing agents.

Hormonal Contraceptives: In a drug-drug interaction study of 15 subjects, coadministration of AYVAKIT 25 mg once daily with an oral contraceptive (levonorgestrel 0.15 mg/ethinyl estradiol 0.03 mg) resulted in a mean ethinyl estradiol AUC ratio of 1.15 (90% confidence interval [CI]: 1.04, 1.28) and a mean ethinyl estradiol Cmax ratio of 1.46 (90% CI: 1.17, 1.81) relative to participants administered the oral contraceptive alone. This increase in ethinyl estradiol Cmax may lead to an increased risk of ethinyl estradiol-related adverse events.

In Vitro Studies

Cytochrome P450 (CYP) Enzymes: In vitro studies indicate that avapritinib is a time-dependent inhibitor as well as an inducer of CYP3A at clinically relevant concentrations.

Avapritinib is an inhibitor of CYP2C9 at clinically relevant concentrations. Avapritinib is not an inhibitor of CYP1A2, CYP2B6, CYP2C8, CYP2C19, or CYP2D6 at clinically relevant concentrations.

Avapritinib is not an inducer of CYP1A2 or CYP2B6. Avapritinib is a substrate of CYP3A.

M499 is an inhibitor of CYP3A, CYP2C8, or CYP2C9 at clinically relevant concentrations. M499 is not an inhibitor of CYP1A2, CYP2B6, CYP2C19, or CYP2D6 at clinically relevant concentrations.

Transporter Systems: Avapritinib is an inhibitor of P-glycoprotein (P-gp), intestinal BCRP, MATE1, MATE2-K, and BSEP, but not an inhibitor of OATP1B1, OATP1B3, OAT1, OAT3, OCT1, or OCT2. Avapritinib is not a substrate of P-gp or BCRP, OAT1, OAT3, OCT1, OCT2, OATP1B1, OATP1B3, MATE1, MATE2-K and BSEP. The effect of M499 on transporter systems is unknown.

13 NONCLINICAL TOXICOLOGY

13.1 Carcinogenesis, Mutagenesis, Impairment of Fertility

Avapritinib was not mutagenic in a 6-month transgenic mouse study up to the highest dose evaluated at 20 mg/kg/day. Avapritinib was not mutagenic in vitro in the bacterial reverse mutation assay (Ames test). Avapritinib was positive in the in vitro chromosome aberration test in human peripheral blood lymphocytes but negative in the in vivo rat bone marrow micronucleus test, and overall non-genotoxic.

There were no direct effects on fertility in rats of either sex in a dedicated fertility and early embryonic development study. Avapritinib may impair spermatogenesis and adversely affect early embryogenesis. Reduction in sperm production and testicular weight were observed in rats and hypospermatogenesis in dogs administered avapritinib at exposure of 8.7 times and 0.5 time the 300 mg human dose, respectively. Avapritinib partitioned into seminal fluids up to 0.2 times the concentration found in human plasma at 300 mg. In female rats there was an increase in pre-implantation loss at exposure of 5.4 times the human exposure at 300 mg and in early resorptions at exposure 2.7 times the human exposure at 300 mg with an overall decrease in viable embryos. Cystic degeneration of corpora lutea and vaginal mucification was also observed in female rats administered avapritinib for up to 6 months at exposure 1.3 times the human exposure based on AUC at the 300 mg dose.

13.2 Animal Toxicology and/or Pharmacology

In repeat dose toxicology studies, administration of avapritinib to rats for up to 28 days and to dogs for up to 3 months resulted in tremors at doses greater than or equal to 100 mg/kg/day or 30 mg/kg/day (approximately 8 and 1.5 times the human exposure based on AUC at the 300 mg dose). Hemorrhage in the brain and spinal cord occurred in dogs at doses greater than or equal to 15 mg/kg/day (approximately 9.0, 1.8, or 0.8 times the human exposure based on AUC at the 25 mg, 200 mg. or 300 mg dose, respectively) and choroid plexus edema in the brain occurred in dogs at doses greater than or equal to 7.5 mg/kg/day (approximately 4.7, 1 or 0.4 times the human exposure based on AUC at the 25 mg, 200 mg or 300 mg dose, respectively), but were not observed in a 9-month study at 5 mg/kg/day.

An in vitro phototoxicity study in 3T3 mouse fibroblasts and an in vivo phototoxicity study in pigmented rats demonstrated that avapritinib has a slight potential for phototoxicity.

14 CLINICAL STUDIES

14.1 Gastrointestinal Stromal Tumors

The efficacy of AYVAKIT was demonstrated in NAVIGATOR (NCT02508532), a multi-center, single-arm, open-label clinical trial. Eligible patients were required to have a confirmed diagnosis of GIST and an ECOG performance status (PS) of 0 to 2. Patients received AYVAKIT 300 mg or 400 mg (1.33 times the recommended dose) orally once daily until disease progression or unacceptable toxicity. The trial initially enrolled patients at a starting dose of 400 mg, which was later reduced to the recommended dose of 300 mg due to toxicity. As there was no apparent difference in overall response rate (ORR) between patients who received 300 mg daily compared to those who received 400 mg daily, these patients were pooled for the efficacy evaluation. The major efficacy outcome measure was ORR based on disease assessment by independent radiological review using modified RECIST v1.1 criteria, in which lymph nodes and bone lesions were not target lesions and progressively growing new tumor nodules within a pre-existing tumor mass was progression. An additional efficacy outcome measure was duration of response (DOR).

Patients with GIST Harboring a PDGFRA Exon 18 Mutation

Patients with unresectable or metastatic GIST harboring a PDGFRA exon 18 mutation were identified by local or central assessment using a PCR- or NGS-based assay. The assessment of efficacy was based on a total of 43 patients, including 38 patients with PDGFRA D842V mutations. The median duration of follow up for patients with PDGFRA exon 18 mutations was 10.6 months (range: 0.3 to 24.9 months).

The study population characteristics were median age of 64 years (range: 29 to 90 years), 67% were male, 67% were White, 93% had an ECOG PS of 0-1, 98% had metastatic disease, 53% had largest target lesion >5 cm, and 86% had prior surgical resection. The median number of prior kinase inhibitors was 1 (range: 0 to 5).

Efficacy results in patients with GIST harboring PDGFRA exon 18 mutations including the subgroup of patients with PDGFRA D842V mutations enrolled in NAVIGATOR are summarized in Table 11.

Table 11. Efficacy Results for Patients with GIST Harboring PDGFRA Exon 18 Mutations in NAVIGATOR
Efficacy Parameter | PDGFRA exon 18 [Exon 18 mutations other than D842V included in this population are: deletion of D842_H845 (n=3); D842Y (n=1); and deletion of D842_H845 with insertion of V (n=1).] N = 43 | PDGFRA D842V N = 38
Overall Response Rate (95% CI) | 84% (69%, 93%) | 89% (75%, 97%)
Complete Response, n (%) | 3 (7%) | 3 (8%)
Partial Response, n (%) | 33 (77%) | 31 (82%)
Duration of Response | n=36 | n=34
Median in months (range) | NR (1.9 [Denotes ongoing response] , 20.3) | NR (1.9, 20.3)
Patients with DOR ≥ 6-months, n (%) [11 patients with an ongoing response were followed < 6 months from onset of response.] | 22 (61%) | 20 (59%)
Abbreviations: CI=confidence interval; NR=not reached

14.2 Advanced Systemic Mastocytosis

The efficacy of AYVAKIT was demonstrated in EXPLORER (NCT02561988) and PATHFINDER (NCT03580655), two multi-center, single-arm, open-label clinical trials. Response-evaluable patients include those with a confirmed diagnosis of AdvSM per World Health Organization (WHO) and deemed evaluable by modified international working group-myeloproliferative neoplasms research and treatment-European competence network on mastocytosis (IWG-MRT-ECNM) criteria at baseline as adjudicated by an independent central committee, who received at least 1 dose of AYVAKIT, had at least 2 post-baseline bone marrow assessments, and had been on study for at least 24 weeks, or had an end of study visit. All enrolled patients had an ECOG performance status (PS) of 0 to 3 and 91% had a platelet count of ≥ 50 × 10^9/L prior to initiation of therapy.

Patients enrolled in EXPLORER received a starting dose of AYVAKIT ranging from 30 mg to 400 mg (0.15 – 2 times the recommended dose) orally once daily. In PATHFINDER, patients were enrolled at a starting dose of 200 mg orally once daily. The efficacy of AYVAKIT in the treatment of AdvSM was based on overall response rate (ORR) in 53 patients with AdvSM dosed at up to 200 mg daily per modified IWG-MRT-ECNM criteria as adjudicated by the central committee. Additional efficacy outcome measures were duration of response (DOR), time to response, and changes in individual measures of mast cell burden.

The median duration of follow up for these patients was 11.6 months (95% confidence interval: 9.9, 16.3).

The study population characteristics were median age of 67 years (range: 37 to 85 years), 58% were male, 98% were White, 68% had an ECOG PS of 0-1, 32% had an ECOG PS of 2-3, 40% had ongoing corticosteroid therapy use for AdvSM at baseline, 66% had prior antineoplastic therapy, 47% had received prior midostaurin, and 94% had a D816V mutation. The median bone marrow mast cell infiltrate was 50%, the median serum tryptase level was 255.8 ng/mL, and the median KIT D816V mutant allele fraction was 12.2%.

Efficacy results in patients with AdvSM enrolled in EXPLORER and PATHFINDER are summarized in Table 12.

Table 12. Efficacy Results for Patients with AdvSM in EXPLORER and PATHFINDER
 | All evaluable patients | ASM | SM-AHN | MCL
Overall Response Rate [Overall Response Rate (ORR) per modified IWG-MRT-ECNM is defined as patients who achieved a CR, CRh or PR (CR + CRh + PR)] , % per modified IWG-MRT-ECNM (95% CI [Clopper–Pearson confidence interval]) | N=53 57 (42, 70) | N=2 100 (16, 100) | N=40 58 (41, 73) | N=11 45 (17, 77)
Complete Remission with full or partial hematologic recovery, % | 28 | 50 | 33 | 9
Partial Remission, % | 28 | 50 | 25 | 36
Clinical Improvement, % | 15 | 0 | 20 | 0
Stable Disease, % | 19 | 0 | 13 | 45
Abbreviations: CI=confidence interval; CR=complete remission; CRh=complete remission with partial recovery of peripheral blood counts; PR=partial remission

For all evaluable patients, the median duration of response was 38.3 months (95% confidence interval: 19, not estimable) and the median time to response was 2.1 months.

In the subgroup of patients with MCL, the efficacy of AYVAKIT was based on complete remission (CR).

14.3 Indolent Systemic Mastocytosis

The efficacy of AYVAKIT was demonstrated in PIONEER (NCT03731260), a randomized, double-blind, placebo-controlled trial conducted in adult patients with Indolent Systemic Mastocytosis (ISM) based on World Health Organization (WHO) classification. Enrolled patients had moderate to severe symptoms despite receiving at least 2 symptom directed therapies. Patients were randomized to receive 25 mg AYVAKIT orally once daily with best supportive care versus placebo with best supportive care. The treatment duration was over a 24-week period, during the randomized portion of the study.

Efficacy was based on the absolute mean change from baseline to Week 24 in the Indolent Systemic Mastocytosis-Symptom Assessment Form (ISM-SAF) total symptom score (TSS). The ISM-SAF is a patient-reported outcome measure assessing ISM signs and symptoms: abdominal pain, nausea, diarrhea, spots, itching, flushing, bone pain, fatigue, dizziness, headache, brain fog. Scores ranged from 0 ("none") to 10 ("worst imaginable"). The item scores were summed to calculate a daily ISM-SAF TSS (range 0-110), with higher scores indicating greater symptom severity. A biweekly average ISM-SAF TSS was used to evaluate efficacy endpoints.

Additional supportive results included the proportion of AYVAKIT-treated patients achieving ≥50% reduction from baseline through Week 24 in TSS compared to placebo. Objective measures of mast cell burden were assessed including the proportion of AYVAKIT-treated patients with a ≥50% reduction from baseline through Week 24 in serum tryptase, peripheral blood KIT D816V allele fraction and bone marrow mast cells.

The median age of the patients who received AYVAKIT was 50 years (range: 18 to 77 years), 71% were female, 77% were White, <1% were Asian, 3% had other race and 19% had missing race. Ethnicities included 4% Hispanic or Latino. KIT D816V mutations were identified in 93% of patients. At baseline, the mean TSS was 50.17 (standard deviation: 19.15), the median serum tryptase level was 38.40 ng/mL, the median KIT D816V mutant allele fraction was 0.39% by ddPCR and the median bone marrow mast cell infiltrate was 7%. Study population characteristics were similar in the placebo group.

The majority of patients who received AYVAKIT (99.3%) or placebo (100%) received concomitant best supportive care at baseline (median of 3 therapies in the AYVAKIT group and 4 in the placebo group). The most common therapies in the AYVAKIT group were H1 antihistamines (97%), H2 antihistamines (66%), leukotriene inhibitors (35%) and cromolyn sodium (30%).

Efficacy results are summarized in Tables 13 and 14.

Table 13. Efficacy Results for Patients with ISM in PIONEER at Week 24
Efficacy Parameter | AYVAKIT (25 mg once daily) + BSC N=141 | Placebo + BSC N=71 | 2-sided p-value
Absolute Mean change in the ISM-SAF TSS [Markov chain Monte Carlo simulation was used to impute the missing values at Baseline or C7D1.]
Change from baseline (95% CI) | -15.33 (-18.36, -12.31) | -9.64 (-13.61, -5.68) | 0.012
Difference from placebo (95% CI) | -5.69 (-10.16, -1.23) |  | 0.012
% of patients achieving ≥50% reduction in the ISM-SAF TSS [Patients with missing values at Baseline or C7D1 were counted in the denominator but not numerator.] (95% CI) | 25 (17.9, 32.8) | 10 (4.1, 19.3) | 0.009
Abbreviations: BSC=best supportive care; CI=confidence interval; ISM-SAF= Indolent Systemic Mastocytosis-Symptom Assessment Form TSS=Total Symptom Score

Table 14. Efficacy Results Related to Mast Cell Burden for Patients with ISM in PIONEER at Week 24
Efficacy Parameter | AYVAKIT (25 mg once daily) + BSC | Placebo + BSC | 2-sided p-value
% of patients with a ≥50% reduction in serum tryptase (95% CI) | N=141 53.9 (45.3, 62.3) | N=71 0 (0.0, 5.1) | <0.0001
% of patients with a ≥50% reduction in peripheral blood KIT D816V allele fraction or undetectable (95% CI) | N=118 67.8 (58.6, 76.1) | N=63 6.3 (1.8, 15.5) | <0.0001
% of patients with a ≥50% reduction in bone marrow mast cells or no aggregates (95% CI) | N=106 52.8 (42.9, 62.6) | N=57 22.8 (12.7, 35.8) | <0.0001
Abbreviations: BSC=best supportive care; CI=confidence interval

To aid in the interpretation of the ISM-SAF TSS absolute mean change from baseline results, the proportion of patients reporting less than or equal to any particular level of change in the ISM-SAF TSS from baseline to Week 24 is depicted in a cumulative distribution function plot as shown in Figure 1.

Figure 1: Cumulative Proportion of Patients with ISM in PIONEER Reporting Change in ISM-SAF TSS From Baseline to Week 24

16 HOW SUPPLIED/STORAGE AND HANDLING

AYVAKIT (avapritinib) tablets are supplied as follows:

25 mg, round, white film-coated tablet with debossed text. One side reads "BLU" and the other side reads "25"; available in bottles of 30 tablets (NDC 72064-125-30).

50 mg, round, white film-coated tablet with debossed text. One side reads "BLU" and the other side reads "50"; available in bottles of 30 tablets (NDC 72064-150-30).

100 mg, round, white film-coated tablet, printed with blue ink "BLU" on one side and "100" on the other side; available in bottles of 30 tablets (NDC 72064-110-30).

200 mg, capsule shaped, white film-coated tablet, printed with blue ink "BLU" on one side and "200" on the other side; available in bottles of 30 tablets (NDC 72064-120-30).

300 mg, capsule shaped, white film-coated tablet, printed with blue ink "BLU" on one side and "300" on the other side; available in bottles of 30 tablets (NDC 72064-130-30).

STORAGE AND HANDLING

Store at 20°C to 25°C (68°F to 77°F); excursions are permitted from 15°C to 30°C (59°F to 86°F) [see USP Controlled Room Temperature].

17 PATIENT COUNSELING INFORMATION

Advise the patient to read the FDA-approved patient labeling (Patient Information).

Intracranial Hemorrhage

Advise patients to contact their healthcare provider immediately if experiencing neurological signs and symptoms that may be associated with intracranial hemorrhage (i.e., severe headache, vomiting, drowsiness, dizziness, confusion, slurred speech, or paralysis) [see Warnings and Precautions (5.1)].

Inform patients with AdvSM of the need to monitor platelet counts before and during treatment [see Warnings and Precautions (5.1)].

Cognitive Effects

Advise patients and caretakers to notify their healthcare provider if they experience new or worsening cognitive symptoms. Advise patients not to drive or operate hazardous machinery if they are experiencing cognitive adverse reactions [see Warnings and Precautions (5.2)].

Photosensitivity

Inform patients that there is a potential risk of photosensitivity reactions with AYVAKIT. Advise patients to limit direct ultraviolet exposure by using sunscreen and protective clothing during treatment with AYVAKIT [see Warnings and Precautions (5.3)].

Embryo-Fetal Toxicity

Advise pregnant women and females of reproductive potential of the potential risk to a fetus. Advise females of reproductive potential to inform their healthcare provider of a known or suspected pregnancy [see Warnings and Precautions (5.4), Use in Specific Populations (8.1)].

Advise females of reproductive potential to use effective contraception during treatment with AYVAKIT and for 6 weeks after the final dose [see Drug Interactions (7.2), Use in Specific Populations (8.3)].

Advise males with female partners of reproductive potential to use effective contraception during treatment with AYVAKIT and for 6 weeks after the final dose [see Use in Specific Populations (8.3), Nonclinical Toxicology (13.1)].

Lactation

Advise women not to breastfeed during treatment with AYVAKIT and for 2 weeks following the final dose [see Use in Specific Populations (8.2)].

Infertility

Advise females of reproductive potential that AYVAKIT may impair fertility at 200 mg or 300 mg [see Use in Specific Populations (8.3), Nonclinical Toxicology (13.1)]. Advise males of reproductive potential that AYVAKIT may decrease sperm production at 200 mg or 300 mg [see Use in Specific Populations (8.3), Nonclinical Toxicology (13.1)].

Drug Interactions

Advise patients and caregivers to inform their healthcare provider of all concomitant medications, including prescription medicines, over-the-counter drugs, vitamins, and herbal products [see Drug Interactions (7.1)].

Administration

Advise patients to take AYVAKIT on an empty stomach, at least 1 hour before or at least 2 hours after a meal [see Dosage and Administration (2.1)].

Manufactured for:

Blueprint Medicines Corporation, Cambridge, MA 02139, USA

PATIENT INFORMATION
AYVAKIT® (aye vah kit)
(avapritinib)
tablets, for oral use

What is AYVAKIT?
AYVAKIT is a prescription medicine used to treat adults with:

- a certain type of stomach, bowel, or esophagus cancer called gastrointestinal stromal tumor (GIST) that cannot be treated with surgery or that has spread to other parts of the body (metastatic), and that is caused by certain abnormal platelet-derived growth factor receptor alpha (PDGFRA) genes. Your healthcare provider will perform a test to make sure that you have this abnormal PDGFRA gene and that AYVAKIT is right for you.
- advanced systemic mastocytosis (AdvSM), including aggressive systemic mastocytosis (ASM), systemic mastocytosis with an associated hematological neoplasm (SM-AHN), and mast cell leukemia (MCL).
  AYVAKIT is not recommended for the treatment of AdvSM in people with low platelet counts (less than 50 × 10^9/L).
- indolent systemic mastocytosis (ISM).
  AYVAKIT is not recommended for the treatment of ISM in people with low platelet counts (less than 50 × 10^9/L).

It is not known if AYVAKIT is safe and effective in children.

Before taking AYVAKIT, tell your healthcare provider about all of your medical conditions, including if you:

- have a history of bulging or weakening of a blood vessel wall (aneurysm) or bleeding in your brain
- history of stroke within the last year
- have low platelet counts
- have or have had liver problems
- are pregnant or plan to become pregnant. AYVAKIT can cause harm to your unborn baby.
  Females who are able to become pregnant:
  - Your healthcare provider should do a pregnancy test before you start treatment with AYVAKIT.
  - You should use effective birth control (contraception) during treatment with AYVAKIT and for 6 weeks after the final dose of AYVAKIT. Talk to your healthcare provider about birth control methods that may be right for you.
  - Tell your healthcare provider right away if you become pregnant or think you may be pregnant during treatment with AYVAKIT.
  Males with female partners who are able to become pregnant should use effective birth control (contraception) during treatment and for 6 weeks after the final dose of AYVAKIT.
- are breastfeeding or plan to breastfeed. It is not known if AYVAKIT passes into your breast milk. Do not breastfeed during treatment with AYVAKIT and for at least 2 weeks after the final dose of AYVAKIT. Talk to your healthcare provider about the best way to feed your baby during this time.

Tell your healthcare provider about all the medicines you take, including prescription and over-the-counter medicines, vitamins, and herbal supplements. AYVAKIT may affect the way other medicines work, and certain other medicines may affect how AYVAKIT works.
Especially tell your healthcare provider if you take:

- estrogen-containing hormonal birth control (contraception)
- medicines that prevent blood clots

How should I take AYVAKIT?

- Take AYVAKIT exactly as your healthcare provider tells you to take it.
- Do not change your dose or stop taking AYVAKIT unless your healthcare provider tells you to.
- AYVAKIT is usually taken 1 time each day.
- Take AYVAKIT tablet(s) on an empty stomach at least 1 hour before or at least 2 hours after a meal.
- If you miss a dose of AYVAKIT, take it as soon as you remember unless your next scheduled dose is due within 8 hours. Take the next dose at your regular time.
- If you vomit after taking a dose of AYVAKIT, do not take an extra dose. Take your next dose at your next scheduled time.

What should I avoid while taking AYVAKIT?

- Do not drive or operate heavy machinery if you have confusion or trouble thinking during treatment with AYVAKIT.
- Your skin may be sensitive to the sun or other forms of light (photosensitivity) during treatment with AYVAKIT. Avoid or limit exposure to direct sunlight, sunlamps, and other sources of ultraviolet radiation during treatment and for 1 week after stopping treatment with AYVAKIT. Use sunscreen or wear clothes that cover your skin if you need to be out in the sun.

What are the possible side effects of AYVAKIT?
AYVAKIT may cause serious side effects, including:

- Bleeding in your brain. Serious bleeding in the brain may happen during treatment with AYVAKIT and may lead to death. Stop taking AYVAKIT and tell your healthcare provider right away if you develop any symptoms such as severe headache, nausea, vomiting, vision changes, drowsiness, dizziness, confusion, or severe weakness on one or more side of your body. Bleeding in the brain has not been seen in people treated with AYVAKIT for ISM.
  If you have AdvSM, your healthcare provider will check your platelet counts before and during treatment with AYVAKIT.
- Cognitive effects. Cognitive side effects can happen during treatment with AYVAKIT and can be severe. Tell your healthcare provider if you develop any new or worsening cognitive symptoms including:

- forgetfulness
- confusion
- getting lost
- trouble thinking
- drowsiness

- trouble staying awake (somnolence)
- word finding problems
- seeing objects or hearing things that are not there (hallucinations)
- change in mood or behavior

- Skin sensitivity to sunlight (photosensitivity). See "What should I avoid while taking AYVAKIT?"

The most common side effects of AYVAKIT in people with GIST include:

- fluid retention or swelling
- nausea
- tiredness or weakness
- trouble thinking
- vomiting
- decreased appetite
- diarrhea

- increased eye tearing
- stomach area (abdominal) pain
- constipation
- rash
- dizziness
- hair color changes
- changes in certain blood tests

The most common side effects of AYVAKIT in people with AdvSM include:

- fluid retention or swelling
- diarrhea
- nausea

- tiredness or weakness
- changes in certain blood tests

The most common side effects of AYVAKIT in people with ISM include:

- swelling around your eyes
- dizziness

- swelling of your arms and legs
- flushing

Your healthcare provider may change your dose, temporarily stop, or permanently stop treatment with AYVAKIT if you develop certain side effects.
AYVAKIT may cause fertility problems in females and males. Talk to your healthcare provider if this is a concern for you.
These are not all of the possible side effects of AYVAKIT.
Call your doctor for medical advice about side effects. You may report side effects to FDA at 1-800-FDA-1088.

How should I store AYVAKIT?

- Store AYVAKIT tablets at room temperature between 68°F to 77°F (20°C to 25°C).

Keep AYVAKIT and all medicines out of the reach of children.

General information about the safe and effective use of AYVAKIT.
Medicines are sometimes prescribed for purposes other than those listed in the Patient Information leaflet. Do not take AYVAKIT for a condition for which it was not prescribed. Do not give AYVAKIT to other people, even if they have the same condition that you have. It may harm them. You can ask your healthcare provider or pharmacist for more information about AYVAKIT that is written for health professionals.

What are the ingredients in AYVAKIT?
Active ingredient: avapritinib
Inactive ingredients: copovidone, croscarmellose sodium, magnesium stearate, and microcrystalline cellulose.
Film coat: polyethylene glycol, polyvinyl alcohol, talc, and titanium dioxide.
Blue printing ink (100 mg, 200 mg and 300 mg tablets only): ammonium hydroxide, black iron oxide, esterified shellac, FD&C blue 1, isopropyl alcohol, n-butyl alcohol, propylene glycol, and titanium dioxide.
Manufactured for: Blueprint Medicines Corporation, Cambridge, MA 02139, USA
© 2023 Blueprint Medicines Corporation. All rights reserved.
For more information, go to www.AYVAKIT.com or call 1-888-258-7768.

This Patient Information has been approved by the U.S. Food and Drug Administration.

Revised: November/2024

PRINCIPAL DISPLAY PANEL - 100 mg Bottle Label

NDC 72064-110-30
30 Tablets

AYVAKIT™
(avapritinib) tablets

100 mg
For Oral Use

Rx only

PRINCIPAL DISPLAY PANEL - 200 mg Bottle Label

NDC 72064-120-30
30 Tablets

AYVAKIT™
(avapritinib) tablets

200 mg
For Oral Use

Rx only

PRINCIPAL DISPLAY PANEL - 300 mg Bottle Label

NDC 72064-130-30
30 Tablets

AYVAKIT™
(avapritinib) tablets

300 mg
For Oral Use

Rx only

PRINCIPAL DISPLAY PANEL - 25 mg Tablet Bottle Label

NDC 72064-125-30
30 Tablets

AYVAKIT™
(avapritinib) tablets

25 mg
For Oral Use

Rx only

PRINCIPAL DISPLAY PANEL - 50 mg Tablet Bottle Label

NDC 72064-150-30
30 Tablets

AYVAKIT™
(avapritinib) tablets

50 mg
For Oral Use

Rx only